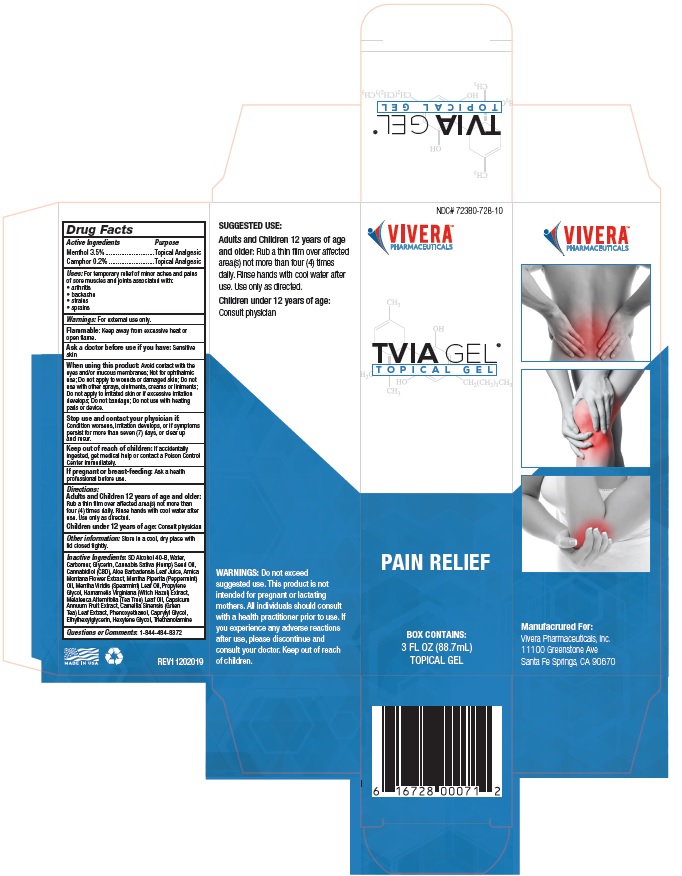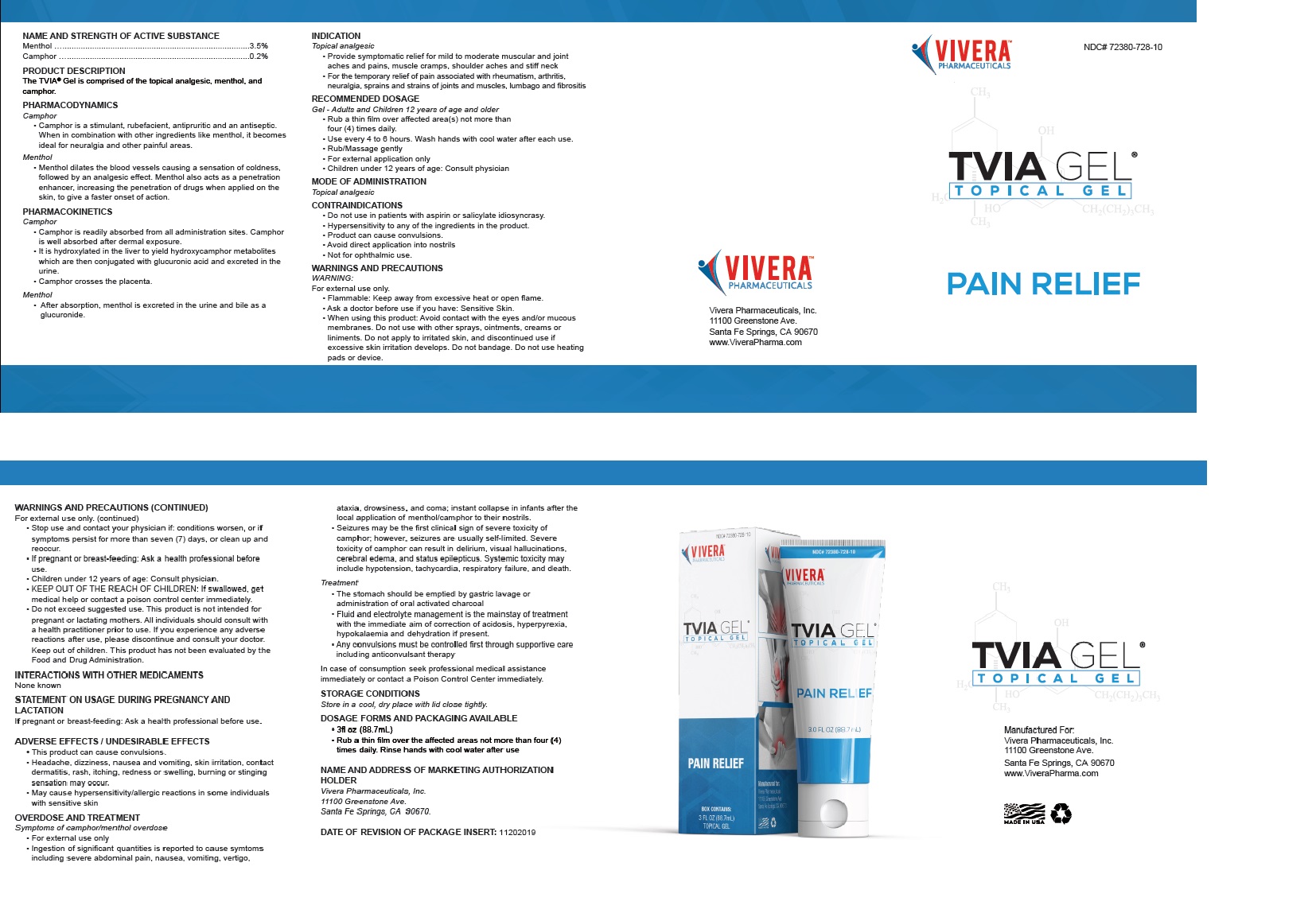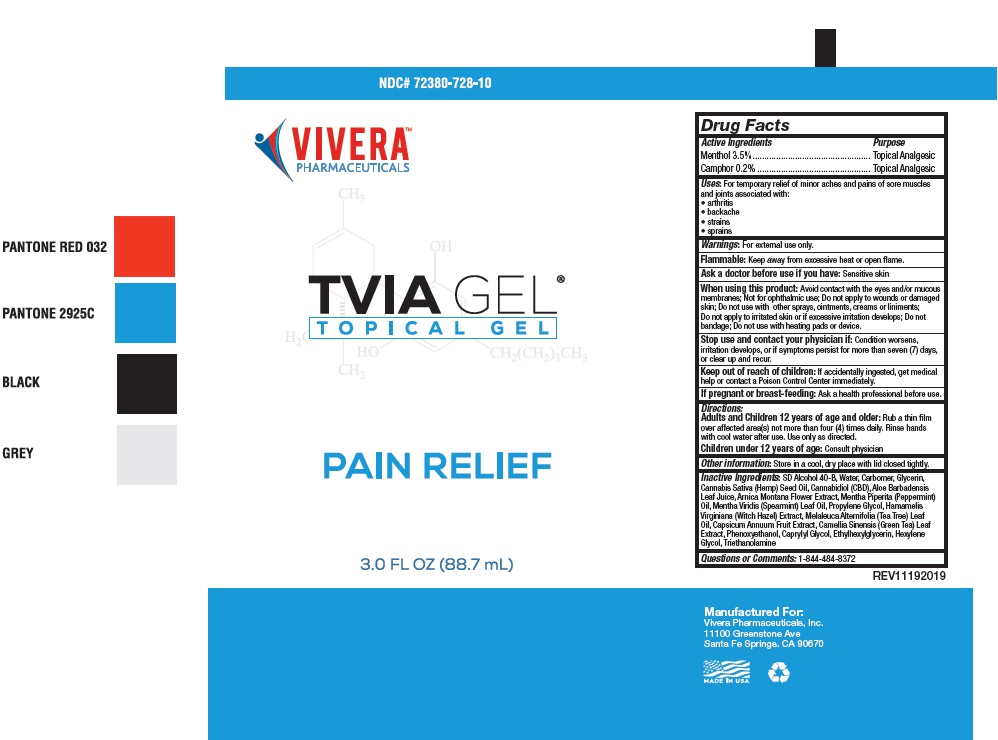 DRUG LABEL: TVIA TOPICAL
NDC: 72380-728 | Form: GEL
Manufacturer: Vivera Pharmaceuticals, Inc.
Category: otc | Type: HUMAN OTC DRUG LABEL
Date: 20191205

ACTIVE INGREDIENTS: MENTHOL 3.5 g/100 mL; CAMPHOR (SYNTHETIC) 0.2 g/100 mL
INACTIVE INGREDIENTS: ALCOHOL; WATER; GLYCERIN; PROPYLENE GLYCOL; CANNABIS SATIVA SEED OIL; CANNABIDIOL; ARNICA MONTANA FLOWER; PEPPERMINT OIL; CARBOXYPOLYMETHYLENE; TROLAMINE; SPEARMINT OIL; GREEN TEA LEAF; ALOE VERA LEAF; HAMAMELIS VIRGINIANA LEAF WATER; TEA TREE OIL; PAPRIKA; PHENOXYETHANOL; CAPRYLIC ALCOHOL; ETHYLHEXYLGLYCERIN; HEXYLENE GLYCOL

TVIA GEL

DRUG FACTS

ACTIVE INGREDIENTS
Menthol 3.5%
Camphor 0.2%

PURPOSE
Menthol ............................Topical Analgesic
Camphor ..........................Topical Analgesic

INDICATIONS AND USAGE

USES: For temporary relief from minor aches and
pains of sore muscles and joints associated with:
arthritis pain • backache • strains • sprains

WARNINGS: For external use only.

OTHER SAFETY INFORMATION

Flammable: Keep away from excessive heat or open flame.

Ask a doctor before use if you have: Sensitive skin

When using this product: Avoid contact with the eyes
and/or mucous membranes • Do not use with other
sprays, ointments, creams or liniments • Do not apply
to irritated skin, & discontinue use if excessive skin
irritation develops • Do not bandage • Do not use
with heating pads or device.

Stop use and contact your physician if: conditions
worsen, or if symptoms persist for more than seven (7)
days, or clear up and reoccur.

If pregnant or breast-feeding: Ask a health
professional before use. Children under 2 years of age:
Consult physician

KEEP OUT OF REACH OF CHILDREN: If swallowed,
get medical help or contact a poison control center
immediately

DOSAGE AND ADMINISTRATION

DIRECTIONS: Use only as directed. Rub a thin film
over the affected areas not more than four (4) times
daily. Rinse hands after use with cool water.

OTHER INFORMATION: Store in a cool, dry place
with lid closed tightly.

INACTIVE INGREDIENTS: Ethyl Alcohol Denatured,
Deionized Water, Glycerin, Propylene Glycol, Cannabis
Sativa Seed Oil (Hemp Seed Oil), Cannabidiol (CBD), Arnica
Montana Flower Extract (Arnica Oil), Mentha Piperita
(Peppermint) Oil, Carbomer, Triethanolamine, Mentha Viridis
(Spearmint) Leaf Oil, Camellia Sinensis Leaf Extract, Aloe
Barbadensis Leaf Extract, Hamamelis Virginiana (Witch
Hazel) Extract, Melaleuca Alternifolia (Tea Tree) Leaf Oil,

Principal Display Package

NDC# 72380-728-10

VIVERA®
PHARMACEUTICALS

TVIA GEL®
T O P I C A L G E L

PAIN RELIEF

BOX CONTAINS:
3 FL OZ (88.7mL)
TOPICAL GEL

6 16728 00071 2

TVIA GEL®
T O P I C A L G E L

SUGGESTED USE: Apply a
small amount topically to
affected area and rub in. Use
every 4 to 6 hours. Safe for
use on adults over 21 years
of age. Wash hands with cool
water after each use.

WARNINGS: Do not exceed
suggested use. This product
is not intended for pregnant
or lactating mothers. All
individuals should consult with
a health practitioner prior
to use. If you experience any
adverse reactions after use,
please discontinue and consult
your doctor. Keep out of reach
of children. This product has
not been evaluated by the
Food and Drug Administration.

VIVERA®
PHARMACEUTICALS

*These statements have not been
evaluated by the Food and Drug
Administration. This product is not
intended to diagnose, treat, cure or
prevent any disease.

VIV-71000-GBX REV20190115

VIVERA®
PHARMACEUTICALS

Manufacrured For:
Vivera Pharmaceuticals, Inc.
11100 Greenstone Ave
Santa Fe Springs, CA 90670

MADE IN USA

Retail Box

Tube

Insert

TVIA Topical Gel by Vivera Pharmaceuticals, Inc.

res